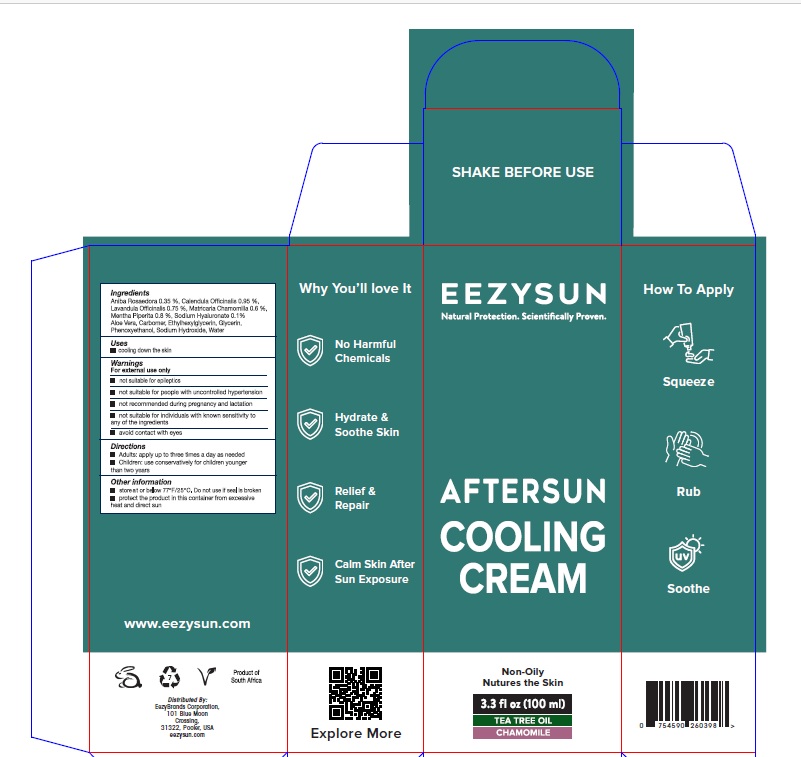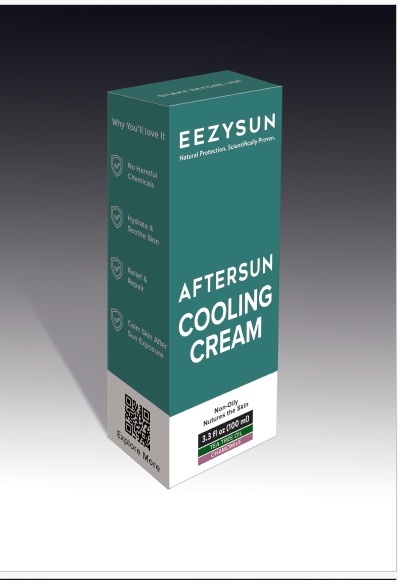 DRUG LABEL: Eezysun After Sun Cooling
NDC: 70116-025 | Form: CREAM
Manufacturer: BIO EARTH MANUFACTURING (PTY) LTD
Category: homeopathic | Type: HUMAN OTC DRUG LABEL
Date: 20250528

ACTIVE INGREDIENTS: BRAZILIAN ROSEWOOD OIL 0.35 g/100 mL; CALENDULA OFFICINALIS FLOWERING TOP 0.95 g/100 mL; LAVENDER OIL 0.75 g/100 mL; MATRICARIA CHAMOMILLA WHOLE 0.6 g/100 mL; PEPPERMINT OIL 0.8 g/100 mL; HYALURONATE SODIUM 0.1 g/100 mL
INACTIVE INGREDIENTS: ALOE VERA LEAF POLYSACCHARIDES; WATER; CARBOMER HOMOPOLYMER, UNSPECIFIED TYPE; ETHYLHEXYLGLYCERIN; GLYCERIN; PHENOXYETHANOL; SODIUM HYDROXIDE

Active ingredients

Aniba Rossadora 0.35 %
Calendula Officinalis 0.95 %
Lavandula Officialls 0.75 %
Matricaria Chamomilla 0.6 %
Mentha Piperita 0.8 %
Sodium Hyaluronate 0.1 %

Purpose

Relaxing, cooling, anti-inflammatory, soothing, relieving

Uses

Cooling down the skin

Warnings

For external use only.

- Not suitable for epileptics
- Not suitable for people with uncontrolled hyper-tension.
- Not recommended during pregnancy and lactation
- Not suitable for individuals with known sensitivity to any of the ingredients.
- Avoid contact with eyes.

Directions

Shake well before use

Adults: Apply up to three times per day as needed

Children: Use conservatively for children younger than two years

Inactive ingredients

Aloe Vera, Aqua, Carbomer, Ethylhexlglycerin, Glycerin, Phenoxyethanol, Sodium Hydroxide

Other information

Store at or below 77⁰ F/25⁰C

Do not use if seal is broken.

product the product in this container from excessive heat and direact sun